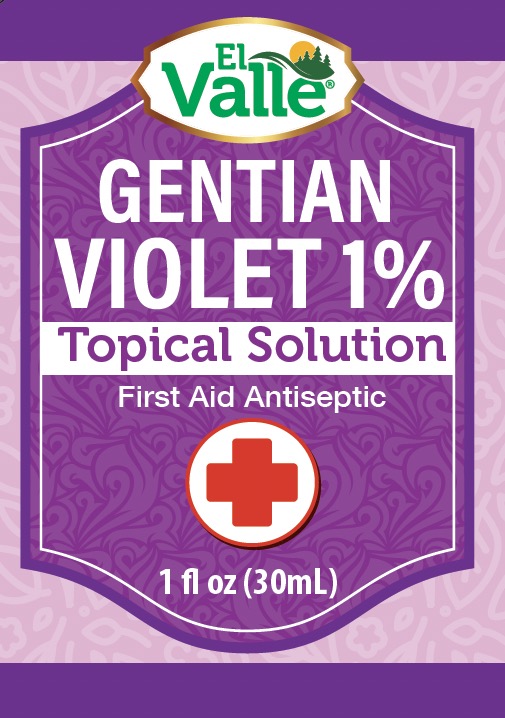 DRUG LABEL: El Valle Gentian Violet
NDC: 55758-373 | Form: LIQUID
Manufacturer: Pharmadel LLC
Category: otc | Type: HUMAN OTC DRUG LABEL
Date: 20251204

ACTIVE INGREDIENTS: GENTIAN VIOLET 10 mg/1 mL
INACTIVE INGREDIENTS: WATER; ALCOHOL

El Valle Gentian Violet 1% (WP)(DA)

Drug Facts

Active Ingredient & Purpose

Gentian Violet 1%

Active ingredient | Purpose
Gentian Violet 1% ............................. | First aid antespetic

Uses

First aid to help prevent infection in

- minor cuts
- scrapes
- burns

Warnings

FOR EXTERNAL USE ONLY.

Do not use

- longer than 1 week, unless directed by a doctor
- in the eyes

Ask a doctor before use if you have

- a deep or puncture wounds
- serious burns
- animal bites

Stop use and consult a doctor if

- conditions persist or gets worse

Keep out of reach of children.

If swallowed, get medical help, or contact a Poison Control Center immediately.

Directions

- clean the affected area
- apply a small amount directly to the affected area 1 to 3 times a day
- may cover area with sterile bandage

Other information

- product will stain clothing and skin
- do not use if clear seal over cap is missing or broken

Warning: Cancer- wwwP65Warnings.ca.gov

Inactive ingredients

alcohol, water